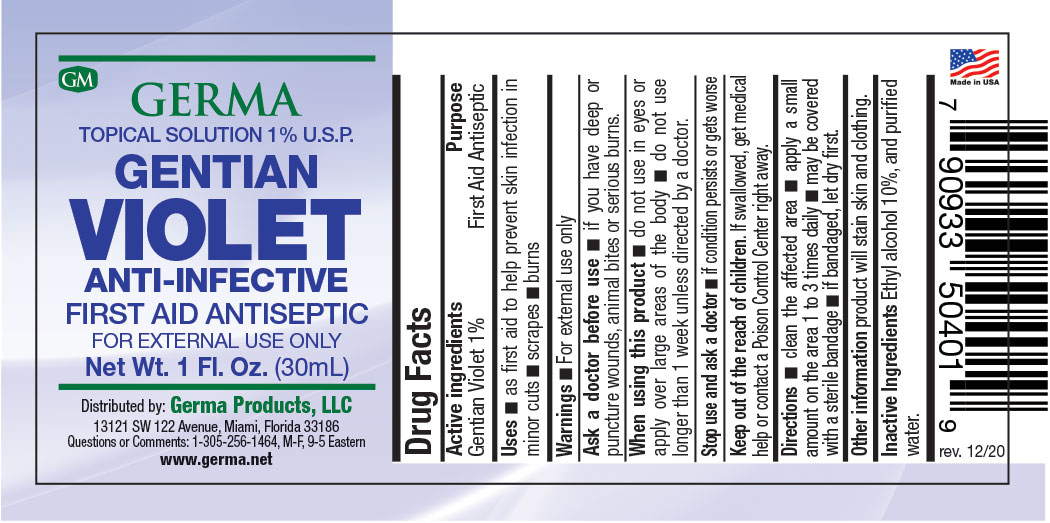 DRUG LABEL: Gentian Violet
NDC: 73635-1219 | Form: LIQUID
Manufacturer: Germa Products, LLC
Category: otc | Type: HUMAN OTC DRUG LABEL
Date: 20251010

ACTIVE INGREDIENTS: GENTIAN VIOLET 10 mg/1 mL
INACTIVE INGREDIENTS: WATER; ALCOHOL

Gentian Violet Antiseptic

Active Ingredient

Gentian Violet 1%

Purpose

First Aid Antiseptic

Uses

As first aid to help prevent skin infection in minor cuts n scrapes n burns
Warnings n For external use only

Warnings

For external use only
Ask a doctor before use. if you have deep or puncture wounds, animal bites or serious burns. When using this product. do not use in eyes or apply over large areas of the body. do not use longer than 1 week unless directed by a doctor.
Stop use and ask a doctor if condition persists or gets worse

Ask a Doctor before use if

You have deep or puncture wounds, animal bites or serious burns.

Keep out of reach of children.

Keep out of the reach of children. If swallowed, get medical
help or contact a Poison Control Center right away.

Directions

Clean the affected area, apply a small amount on the area 1 to 3 times daily. May be covered with a sterile bandage. If bandaged, let dry first.

Other Information

Product will stain skin and clothing.

Inactive Ingredients

Ethyl alcohol 10%, and purified water.

Questions or Comments

1-305-256-1464

Principal Display Panel

Gentian Violet